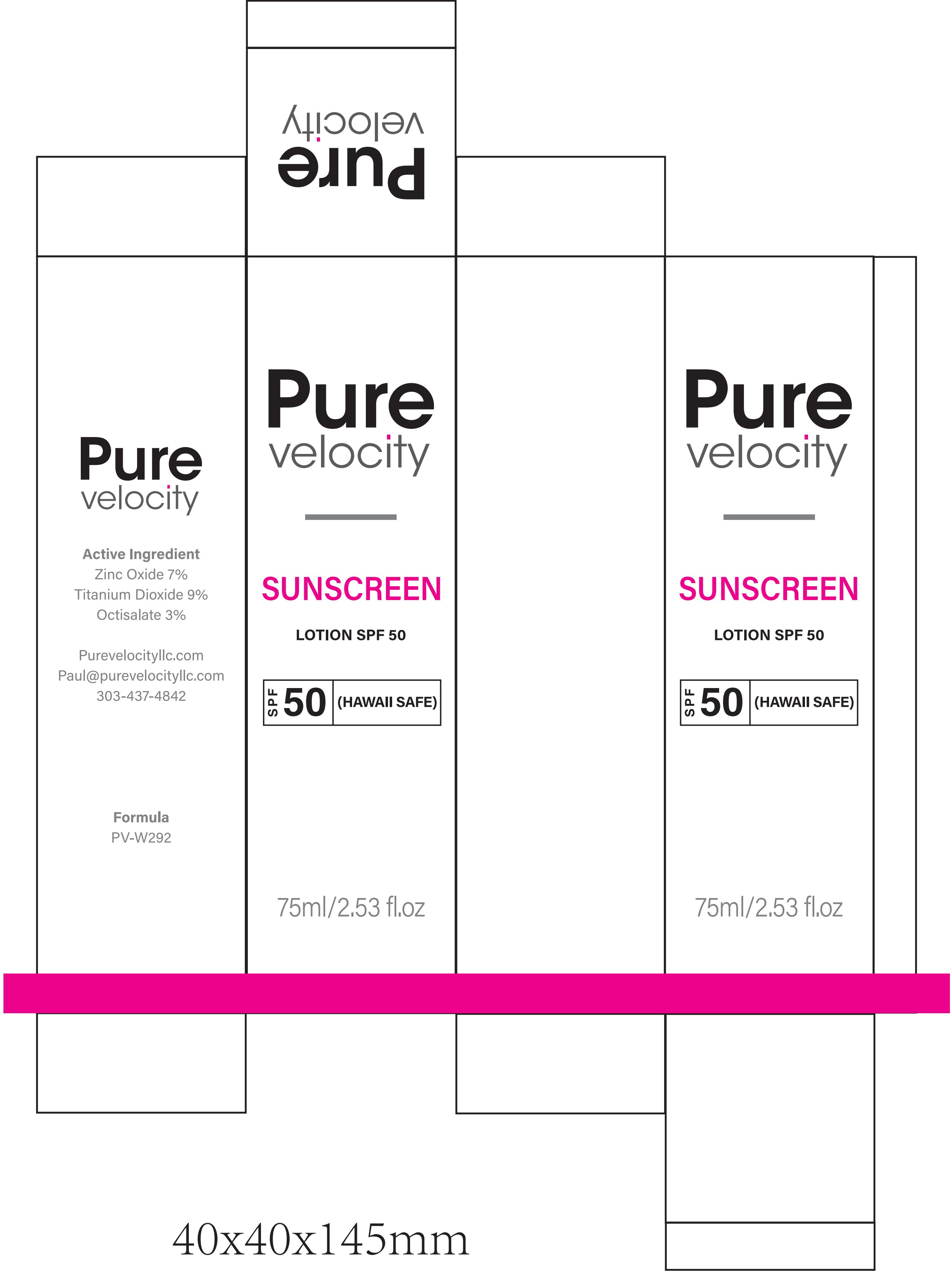 DRUG LABEL: Pure velocity SUNSCREEN SPF 50
NDC: 60771-0038 | Form: CREAM
Manufacturer: Guangzhou Haishi Biological Technology Co., Ltd.
Category: otc | Type: HUMAN OTC DRUG LABEL
Date: 20250930

ACTIVE INGREDIENTS: HOMOSALATE 3.75 g/100 mL; OCTOCRYLENE 6 g/100 mL; OCTINOXATE 3 g/100 mL
INACTIVE INGREDIENTS: GLYCERIN; WATER

Active Ingredients

OCTOCRYLENE
HOMOSALATE
OCTINOXATE

Purpose

SUNSCREEN

Uses

If used as directed with other sun protection measures(see Directions)，
decreases the risk of skin cancer and early skin aging caused by the sun.

Warnings

For external use only

Stop Use

Rinse with wate to remove.
Stop use and ask doctor if rash occurs.

Do not use on damaged or broken skin.

When Using

When using this product keep out of eyes.

Keep Out Of Reach Of Children

Dosage & administration

Squeeze out an appropriate amount of Sunscreen and spread evenly on skin.

Inactive ingredients

Water
Glycerin
C12-15 Alkyl Benzoate
Dimethicone
Isododecane
Butyloctyl Salicylate
Propanediol
Stearic Acid
PEG-100 Stearate
Sorbitan Stearate
Niacinamide
Ceramide NP
Ceramide AP
Ceramide EOP
Sorbitan Isostearate
Carbomer
Cetearyl Alcohol
Ceteareth-20
Triethoxycaprylylsilane
Dimethiconol
Sodium Citrate
Sodium Lauroyl Lactylate
Sodium Dodecylbenzenesulfonate
Myristic Acid
Sodium Hyaluronate
Cholesterol
Aluminum Hydroxide
Palmitic Acid
Phenoxyethanol
Chlorphenesin
Hydroxyethyl Acrylate / Sodium Acryloyldimethyl Taurate Copolymer
Caprylyl Glycol
Citric Acid
Panthenol
Xanthan Gum
Phytosphingosine
Polyhydroxystearic Acid
Polysorbate 60
Ethylhexylglycerin